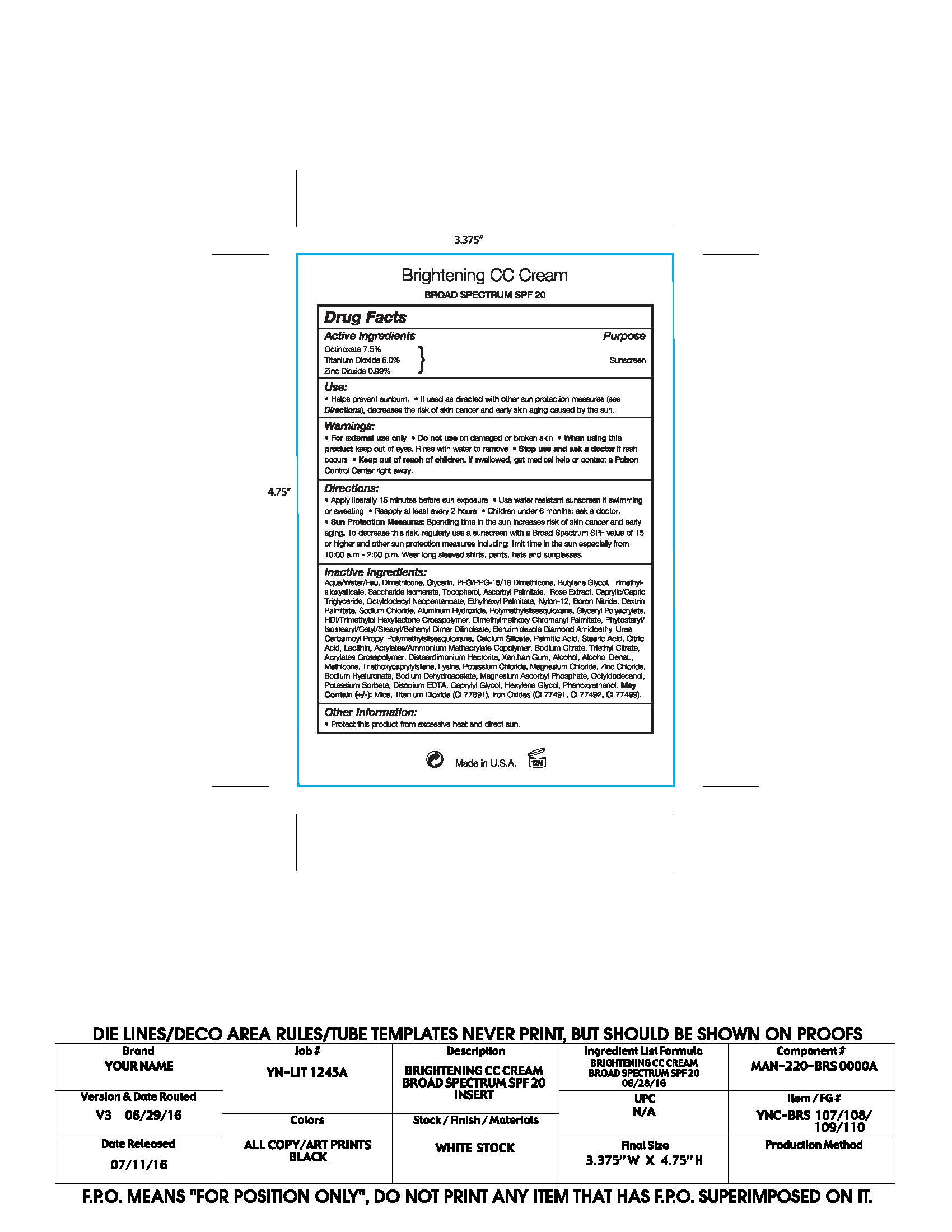 DRUG LABEL: Your Name Cosmetics Brightening CC Cream Broad Spectrum SPF 20
NDC: 59735-160 | Form: LOTION
Manufacturer: Mana Products
Category: otc | Type: HUMAN OTC DRUG LABEL
Date: 20170222

ACTIVE INGREDIENTS: OCTINOXATE 7.5 g/100 g; TITANIUM DIOXIDE 5 g/100 g; ZINC OXIDE 0.99 g/100 g
INACTIVE INGREDIENTS: WATER; DIMETHICONE; GLYCERIN; PEG/PPG-18/18 DIMETHICONE; BUTYLENE GLYCOL; TRIMETHYLSILOXYSILICATE (M/Q 0.6-0.8); SACCHARIDE ISOMERATE; TOCOPHEROL; ASCORBYL PALMITATE; CAPRYLIC/CAPRIC/LAURIC TRIGLYCERIDE; OCTYLDODECYL NEOPENTANOATE; ETHYLHEXYL PALMITATE; NYLON-12; BORON NITRIDE; DEXTRIN PALMITATE (CORN; 20000 MW); SODIUM CHLORIDE; ALUMINUM HYDRIDE; POLYMETHYLSILSESQUIOXANE (11 MICRONS); DIMETHYLMETHOXY CHROMANYL PALMITATE; PHYTOSTERYL/ISOSTEARYL/CETYL/STEARYL/BEHENYL DIMER DILINOLEATE; CALCIUM SILICATE; PALMITIC ACID; STEARIC ACID; CITRIC ACID MONOHYDRATE; LECITHIN, SOYBEAN; SODIUM CITRATE; TRIETHYL CITRATE; DISTEARDIMONIUM HECTORITE; XANTHAN GUM; ALCOHOL; METHICONE (20 CST); TRIETHOXYCAPRYLYLSILANE; LYSINE; POTASSIUM CHLORIDE; MAGNESIUM CHLORIDE; ZINC CHLORIDE; SODIUM DEHYDROACETATE; MAGNESIUM ASCORBYL PHOSPHATE; OCTYLDODECANOL; POTASSIUM SORBATE; DISODIUM EDTA-COPPER; CAPRYLYL GLYCOL; HEXYLENE GLYCOL; PHENOXYETHANOL

DRUG FACTS

Active Ingredients

Octinoxate 7.5%

Titanium Dioxide 5.00%

Zinc Oxide 0.99%

Use

- Helps prevent sunburn.
- If used as directed with other sun protection measures (see Directions), decreases the risk of skin cancer and early skin aging caused by the sun.

Warnings

- For external use only
- Do not use on damaged or broken skin
- When using this product keep out of eyes. Rinse with water to remove.
- Stop use and ask a docor if rash occurs
- Keep out of reach of children. If swalled, get medical help or contact a Poison Control Center right away.

Directions

- Apply liberally 15 minutes before sun exposure
- Reapply at least every 2 hours
- Use water resistant sunscreen if swimming or sweathing
- Sun Protection Measures: Spending time in the sun decreases risk of skin cancer and early again. To decrease this risk, regulaory use a sunscreen with a Broad Spectrum SPF value of 15 or higher and other sun protection measures including: Limit time in the sun especially from 10:00 am - 2:00 pm. Wear long sleeved shirts, pants, hats and sunglasses.
- Children under 6 months: ask a doctor

Inactive Ingredients

Aqua/Water/Eau, Dimethicone, Glycerin, PEG/PPG-18/18 Dimethicone,
Butylene Glycol, Trimethylsiloxysilicate , Saccharide Isomerate, Tocopherol, Ascorbyl Palmitate,
Rose Extract, Caprylic/Capric Triglyceride, Octyldodecyl Neopentanoate , Ethylhexyl Palmitate,
Nylon-12, Boron Nitride, Dextrin Palmitate, Sodium Chloride, Aluminum Hydroxide, Polymethylsilsesquioxane, Glyceryl Polyacrylate, HDI/Trimethylol Hexyllactone Crosspolymer, Dimethylmethoxy Chromanyl Palmitate, Phytosteryl/Isostearyl/Cetyl/Stearyl/Behenyl Dimer Dilinoleate,
Benzimidazole Diamond Amidoethyl Urea Carbamoyl Propyl Polymethylsilsesquioxane, Calcium Silicate,
Palmitic Acid, Stearic Acid, Citric Acid , Lecithin, Acrylates/Ammonium Methacrylate Copolymer,
Sodium Citrate, Triethyl Citrate , Acrylates Crosspolymer, Disteardimonium Hectorite, Xanthan Gum, Alcohol, Alcohol Denat., Methicone, Triethoxycaprylylsilane, Lysine, Potassium Chloride, Magnesium Chloride, Zinc Chloride, Sodium Hyaluronate, Sodium Dehydroacetate, Magnesium Ascorbyl Phosphate, Octyldodecanol, Potassium Sorbate, Disodium EDTA, Caprylyl Glycol, Hexylene Glycol, Phenoxyethanol May Contain (+/-):
Mica, Titanium Dioxide (CI 77891), Iron Oxides (CI 77491, CI 77492, CI 77499)

Other Information

- Protect this product form excessive heat and direct sun